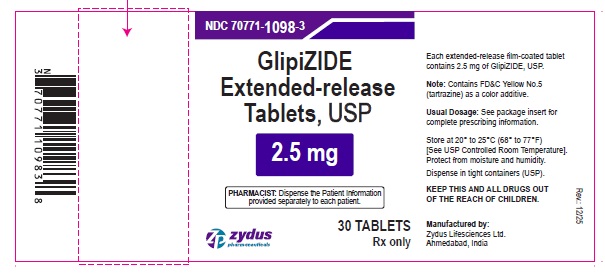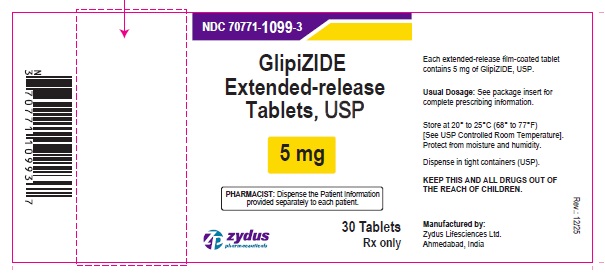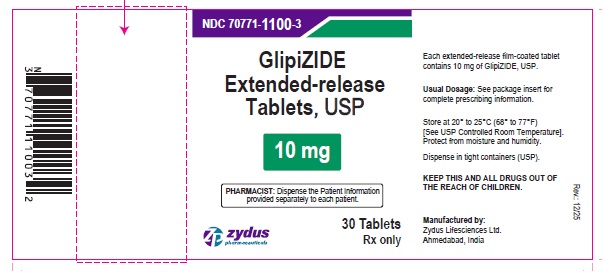 DRUG LABEL: Glipizide
NDC: 70771-1098 | Form: TABLET, EXTENDED RELEASE
Manufacturer: Zydus Lifesciences Limited
Category: prescription | Type: HUMAN PRESCRIPTION DRUG LABEL
Date: 20260105

ACTIVE INGREDIENTS: GLIPIZIDE 2.5 mg/1 1
INACTIVE INGREDIENTS: ACETYLTRIBUTYL CITRATE; ALUMINUM OXIDE; AMMONIA; BUTYL ALCOHOL; FD&C YELLOW NO. 5; FERROSOFERRIC OXIDE; HYDROXYETHYL CELLULOSE (2000 CPS AT 1%); HYDROXYPROPYL CELLULOSE, UNSPECIFIED; HYPROMELLOSES; ISOPROPYL ALCOHOL; LACTOSE MONOHYDRATE; MAGNESIUM STEARATE; METHACRYLIC ACID - METHYL METHACRYLATE COPOLYMER (1:1); POLYETHYLENE GLYCOL, UNSPECIFIED; PROPYLENE GLYCOL; SHELLAC; SILICON DIOXIDE; TITANIUM DIOXIDE

Glipizide Extended-Release Tablets

PACKAGE LABEL.PRINCIPAL DISPLAY PANEL

NDC 70771-1098-3 in bottle of 30 tablets

Glipizide ER Tablets USP, 2.5 mg

Rx only

30 tablets

NDC 70771-1099-3 in bottle of 30 tablets

Glipizide ER Tablets USP, 5 mg

Rx only

30 tablets

NDC 70771-1100-3 in bottle of 30 tablets

Glipizide ER Tablets USP, 10 mg

Rx only

30 tablets